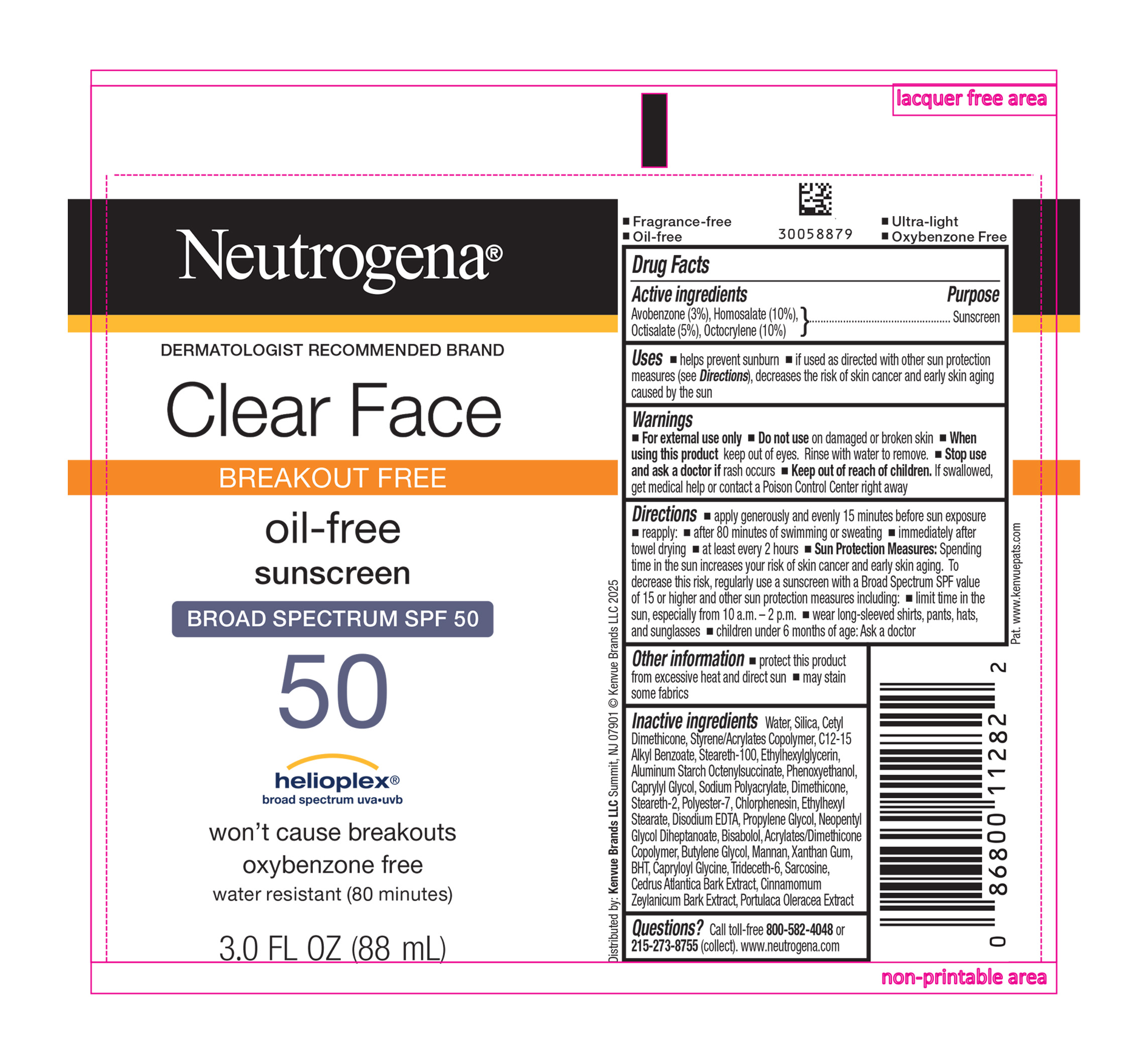 DRUG LABEL: Neutrogena Clear Face Breakout Free oil Free Sunscreen Broad Spectrum SPF 50
NDC: 69968-0662 | Form: LOTION
Manufacturer: Kenvue Brands LLC
Category: otc | Type: HUMAN OTC DRUG LABEL
Date: 20251106

ACTIVE INGREDIENTS: AVOBENZONE 30 mg/1 mL; HOMOSALATE 100 mg/1 mL; OCTISALATE 50 mg/1 mL; OCTOCRYLENE 100 mg/1 mL
INACTIVE INGREDIENTS: SILICON DIOXIDE; CETYL DIMETHICONE 25; BUTYL METHACRYLATE/METHYL METHACRYLATE/METHACRYLIC ACID/STYRENE CROSSPOLYMER; ALKYL (C12-15) BENZOATE; WATER; STEARETH-100; ETHYLHEXYLGLYCERIN; ALUMINUM STARCH OCTENYLSUCCINATE; PHENOXYETHANOL; CAPRYLYL GLYCOL; DIMETHICONE; STEARETH-2; POLYESTER-7; CHLORPHENESIN; ETHYLHEXYL STEARATE; EDETATE DISODIUM; PROPYLENE GLYCOL; NEOPENTYL GLYCOL DIHEPTANOATE; LEVOMENOL; BUTYLENE GLYCOL; YEAST MANNAN; XANTHAN GUM; BUTYLATED HYDROXYTOLUENE; CAPRYLOYL GLYCINE; CINNAMON BARK OIL; TRIDECETH-6; CEDRUS ATLANTICA BARK; SARCOSINE; PURSLANE; 2-ETHYLHEXYL ACRYLATE, METHACRYLATE, METHYL METHACRYLATE, OR BUTYL METHACRYLATE/HYDROXYPROPYL DIMETHICONE COPOLYMER (30000-300000 MW)

Neutrogena® Clear Face BREAKOUT FREE oil-free sunscreen BROAD SPECTRUM SPF 50

Drug Facts

ACTIVE INGREDIENT

Active Ingredients | Purpose
Avobenzone 3% | Sunscreen
Homosalate 10% | Sunscreen
Octisalate 5% | Sunscreen
Octocrylene 10% | Sunscreen

Uses

- helps prevent sunburn
- if used as directed with other sun protection measures (see Directions), decreases the risk of skin cancer and early skin aging caused by the sun

Warnings

- For external use only

- Do not use on damaged or broken skin

- When using this product keep out of eyes. Rinse with water to remove

- Stop use and ask a doctor if rash occurs

- Keep out of reach of children. If swallowed, get medical help or contact a Poison Control Center right away

Directions

- apply generously and evenly 15 minutes before sun exposure
- reapply:
  - after 80 minutes of swimming or sweating
  - immediately after towel drying
  - at least every 2 hours
- Sun Protection Measures. Spending time in the sun increases your risk of skin cancer and early skin aging. To decrease this risk, regularly use a sunscreen with a Broad Spectrum SPF value of 15 or higher and other sun protection measures including:
  - limit time in the sun, especially from 10 a.m. - 2 p.m.
  - wear long-sleeved shirts, pants, hats, and sunglasses
- children under 6 months of age: Ask a doctor

Other Information

- protect this product from excessive heat and direct sun
- may stain some fabrics

Inactive Ingredients

Water, Silica, Cetyl Dimethicone, Styrene/Acrylates Copolymer, C12-15 Alkyl Benzoate, Steareth-100, Ethylhexylglycerin, Aluminum Starch Octenylsuccinate, Phenoxyethanol, Caprylyl Glycol, Sodium Polyacrylate, Dimethicone, Steareth-2, Polyester-7, Chlorphenesin, Ethylhexyl Stearate, Disodium EDTA, Propylene Glycol, Neopentyl Glycol Diheptanoate, Bisabolol, Acrylates/Dimethicone Copolymer, Butylene Glycol, Mannan, Xanthan Gum, BHT, Capryloyl Glycine, Trideceth-6, Sarcosine, Cedrus Atlantica Bark Extract, Cinnamomum Zeylanicum Bark Extract, Portulaca Oleracea Extract

Questions?

Call toll-free 800-582-4048 or 215-273-8755 (collect). www.neutrogena.com

Distributed by:

Kenvue Brands LLC
Summit, NJ 07901

PRINCIPAL DISPLAY PANEL - 88 mL Tube Label

Neutrogena®

DERMATOLOGIST RECOMMENED BRAND

Clear Face

BREAKOUT FREE

oil-free
sunscreen
BROAD SPECTRUM SPF 50

50

helioplex®
broad spectrum uva.uvb

won't cause breakouts
oxybenzone free
water resistant (80 minutes)

3.0 FL OZ (88 mL)